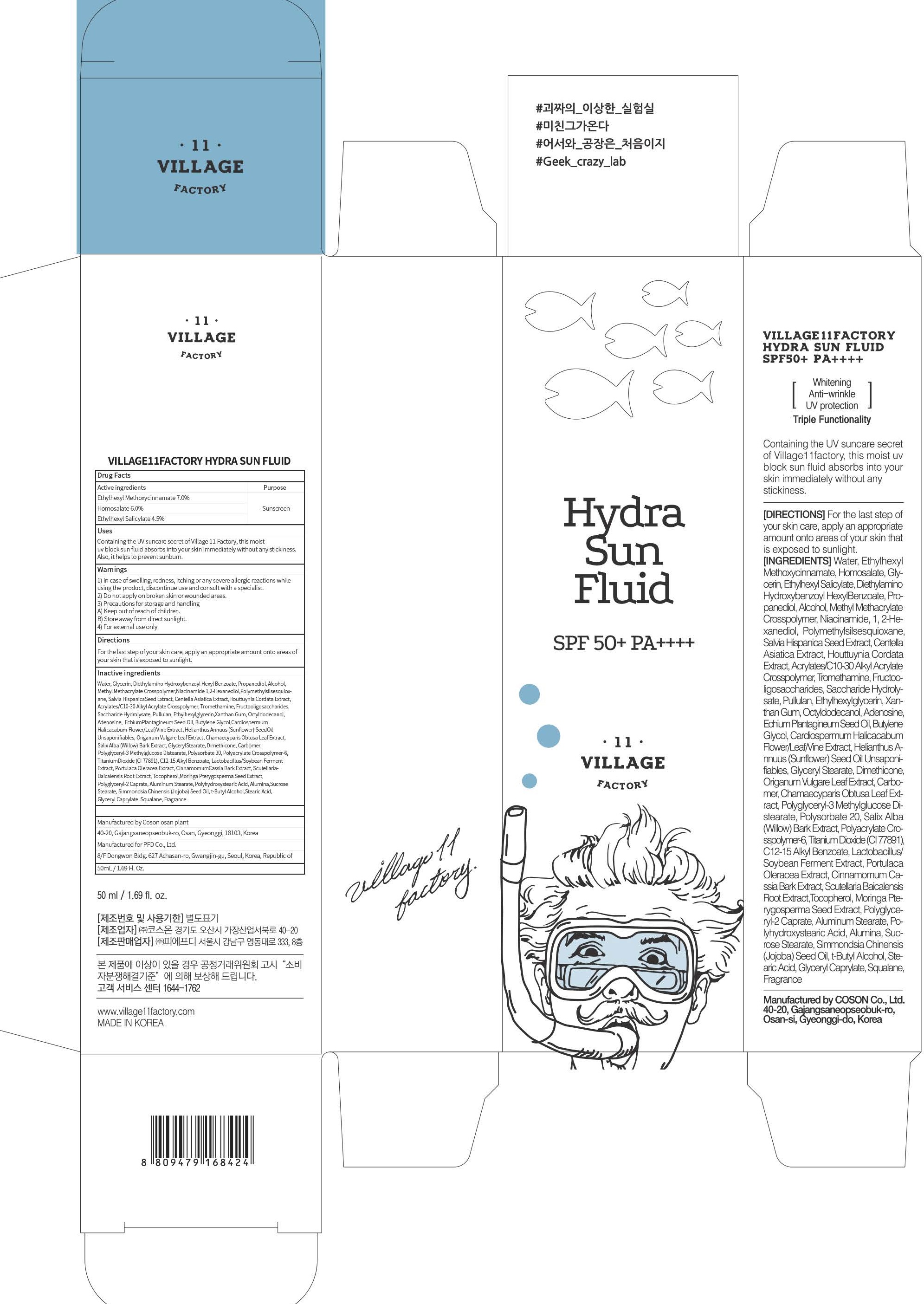 DRUG LABEL: VILLAGE11FACTORY HYDRA SUN FLUID
NDC: 72470-020 | Form: CREAM
Manufacturer: PFD Co.,Ltd.
Category: otc | Type: HUMAN OTC DRUG LABEL
Date: 20180807

ACTIVE INGREDIENTS: Octinoxate 3.50 g/50 mL; Homosalate 3.00 g/50 mL; Octisalate 2.25 g/50 mL
INACTIVE INGREDIENTS: Water; Glycerin

ACTIVE INGREDIENT

Active ingredients: Ethylhexyl Methoxycinnamate 7.0%, Homosalate 6.0%, Ethylhexyl Salicylate 4.5%

INACTIVE INGREDIENT

Inactive ingredients:

Water, Glycerin, Diethylamino Hydroxybenzoyl Hexyl Benzoate, Propanediol, Alcohol,Methyl Methacrylate Crosspolymer,Niacinamide 1,2-Hexanediol,Polymethylsilsesquioxane, Salvia HispanicaSeed Extract, Centella Asiatica Extract,Houttuynia Cordata Extract, Acrylates/C10-30 Alkyl Acrylate Crosspolymer, Tromethamine, Fructooligosaccharides, Saccharide Hydrolysate, Pullulan, Ethylhexylglycerin,Xanthan Gum, Octyldodecanol, Adenosine, EchiumPlantagineum Seed Oil, Butylene Glycol,Cardiospermum Halicacabum Flower/Leaf/Vine Extract, Helianthus Annuus (Sunflower) SeedOil Unsaponifiables, Origanum Vulgare Leaf Extract, Chamaecyparis Obtusa Leaf Extract, Salix Alba (Willow) Bark Extract, GlycerylStearate, Dimethicone, Carbomer, Polyglyceryl-3 Methylglucose Distearate, Polysorbate 20, Polyacrylate Crosspolymer-6, TitaniumDioxide (CI 77891), C12-15 Alkyl Benzoate, Lactobacillus/Soybean Ferment Extract, Portulaca Oleracea Extract, CinnamomumCassia Bark Extract, Scutellaria Baicalensis Root Extract, Tocopherol,Moringa Pterygosperma Seed Extract, Polyglyceryl-2 Caprate,Aluminum Stearate, Polyhydroxystearic Acid, Alumina,Sucrose Stearate, Simmondsia Chinensis (Jojoba) Seed Oil, t-Butyl Alcohol,Stearic Acid, Glyceryl Caprylate, Squalane,Fragrance

PURPOSE

Purpose: Sunscreen

WARNINGS

1) In case of swelling, redness, itching or any severe allergic reactions while using the product, discontinue use and consult with a specialist.

2) Do not apply on broken skin or wounded areas.

3) Precautions for storage and handling A) Keep out of reach of children. B) Store away from direct sunlight.

4) For external use only

DESCRIPTION

Uses:

Containing the UV suncare secret of Village 11 Factory, this moist uv block sun fluid absorbs into your skin immediately without any stickiness. Also, it helps to prevent sunburn.

Directions:

For the last step of your skin care, apply an appropriate amount onto areas of your skin that is exposed to sunlight.